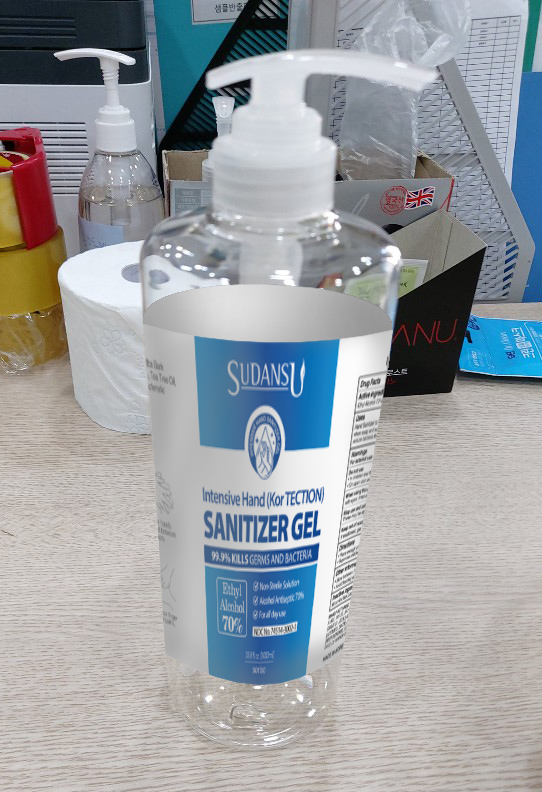 DRUG LABEL: SUDANSU Hand Sanitizer
NDC: 69969-501 | Form: GEL
Manufacturer: Soriso
Category: otc | Type: HUMAN OTC DRUG LABEL
Date: 20201014

ACTIVE INGREDIENTS: ALCOHOL 70 g/100 mL
INACTIVE INGREDIENTS: GLYCERIN; WATER

Drug Facts

ACTIVE INGREDIENT

Alcohol

INACTIVE INGREDIENT

Glycerin, Carbomer, etc.

PURPOSE

Antiseptic

KEEP OUT OF REACH OF THE CHILDREN

INDICATIONS AND USAGE

For the external use only

WARNINGS

For external use only.

Flammable, keep away from fire or flame.

When using this product keep out of eyes. If contact with eyes occurs, rinse promptly and thoroughly with water.

Stop use and ask a doctor if significant irritation or sensitization develops.

Keep out of reach of children. If swallowed, get medical help or contact a Poison Control Center right away.

DOSAGE AND ADMINISTRATION

Put enough product in your palm to cover your hands and rub